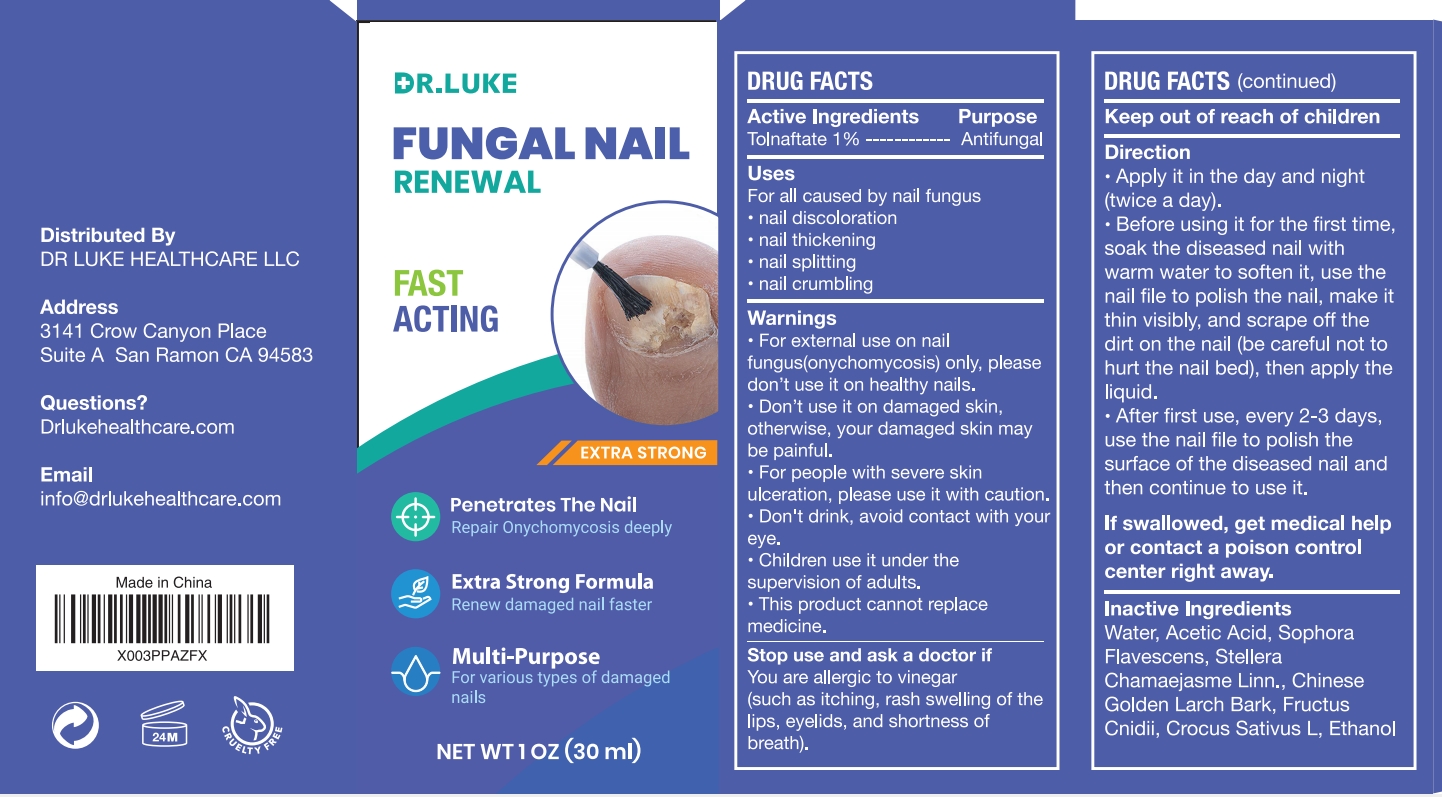 DRUG LABEL: Dr. Luke FUNGAL NAIL RENEWAL
NDC: 87147-005 | Form: LIQUID
Manufacturer: DANOUS LAND FLOOW LLC
Category: otc | Type: HUMAN OTC DRUG LABEL
Date: 20251110

ACTIVE INGREDIENTS: TOLNAFTATE 1 g/100 mL
INACTIVE INGREDIENTS: WATER; ACETIC ACID; SOPHORA FLAVESCENS ROOT; STELLERA CHAMAEJASME WHOLE; PSEUDOLARIX AMABILIS BARK; CROCUS SATIVUS WHOLE; CNIDIUM SEED; ALCOHOL

ACTIVE INGREDIENT

Tolnaftate 1%

PURPOSE

Antifungal Disinfectant Treatment Solution

INDICATIONS AND USAGE

For all caused by nail fungus
nail discoloration
nail thickening
nail splitting
nail crumbling

WARNINGS

- For external use on nail
- fungus(onychomycosis) only, pleasedon't use it on healthy nails
- Don't use it on damaged skin,otherwise, your damaged skin maybe painful.
- For people with severe skinulceration, please use it with caution.
- Don't drink, avoid contact with your eye
- Children use it under thesupervision of adults.
- This product cannot replacemedicine.

DO NOT USE

- On damaged skin(cuts, abrasions, eczema, sunburn).
- If you are allergic to any of the ingredients in this product.
- If you are pregnant or breastfeeding.

WHEN USING

fungal infection itching

STOP USE

You are allergic to vinegarsuch as itching, rash swelling of thelips, eyelids, and shortness ofbreath

ASK DOCTOR/PHARMACIST

You are allergic to vinegarsuch as itching, rash swelling of thelips, eyelids, and shortness ofbreath

Keep out of reach of children.

INSTRUCTIONS FOR USE

- Apply it in the day and night(twice a day).
- Before using it for the first time.soak the diseased nail withwarm water to soften it, use thenail file to polish the nail, make itthin visibly, and scrape off thedirt on the nail (be careful not tohurt the nail bed), then apply the liquid.
- After first use, every 2-3 daysuse the nail file to polish thesurface of the diseased nail andthen continue to use it.
- lf swallowed, get medical helpor contact a poison controlcenter right away.

INACTIVE INGREDIENT

Water, Acetic Acid, SophoraFlavescens，Stellera Chamaejasme whole, ChineseGolden Larch Bark, FructusCnidii, Crocus Sativus Whole, Ethanol,Cnidium Seed, Alcohol

- Do not use if glued carton end flaps are open or if the tube seal is broken.
- Store at 68°-77°F (20°-25C).
- Keep container tightly closed

DOSAGE AND ADMINISTRATION

Apply it in the day and night (twice a day)